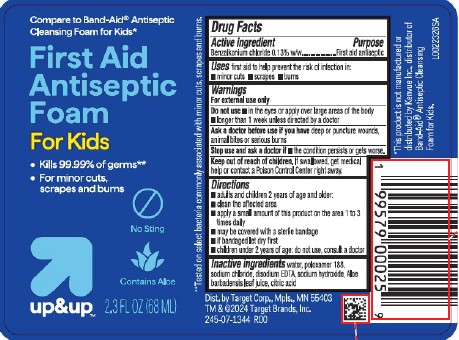 DRUG LABEL: Benzalkonium chloride
NDC: 11673-681 | Form: AEROSOL, FOAM
Manufacturer: Target Corporation
Category: otc | Type: HUMAN OTC DRUG LABEL
Date: 20260218

ACTIVE INGREDIENTS: BENZALKONIUM CHLORIDE 1.3 mg/1 mL
INACTIVE INGREDIENTS: WATER; POLOXAMER 188; SODIUM CHLORIDE; EDETATE DISODIUM; SODIUM HYDROXIDE; ALOE VERA LEAF JUICE; CITRIC ACID MONOHYDRATE

Up & Up D81.000/D81AA
First Aid Antiseptic Foam

Active ingredient

Benzalkonium chloride 0.13% w/w

Purpose

First aid antiseptic

Uses

first aid to help prevent the risk of infection in:

- minor cuts
- scrapes
- burns

Warnings

For external use only

Do not use

- in the eyes or apply over large areas of the body
- longer than 1 week unless directed by a doctor

Ask a doctor before use if you have

deep or puncture wounds, animal bites or serious burns

Stop use and ask a doctor if

- the condition persists or gets worse.

Keep out of reach of children.

If swallowed, get medical help or contact a Poison Control Center right away.

Directions

- adults and children 2 years of age and older:
- clean the affected area
- apply a small amount of this product on the area 1 to 3 times daily
- may be covered with a sterile bandage
- if bandaged let dry first
- children under 2 years of age: do not use, consult a doctor

Inactive ingredients

water, poloxamer 188, sodium chloride, disodium EDTA, sodium hydroxide, Aloe barbadensis leaf juice, citric acid

ADVERSE REACTION

Dist. by Target Corp., Mpls., MN 55403

TM & ©2024 Target Brands, Inc.

Disclaimers

*This product is not manufactured or distributed by Kenvue Inc., distributor of Band-Aid®Antiseptic Cleansing Foam for Kids.

**Tested on select bacteria commonly associated with minor cuts, scrapes and burns.

PRINCIPAL DISPLAY PANEL

Compare to Band-Aid®Antiseptic Cleansing Foam for Kids*

First Aid Antiseptic Foam

For Kids

- Kills 99.99% of germs**
- For minor cuts, scrapes and burns

No Sting

Contains Aloe

up & up™

2.3 FL OZ (68 mL)